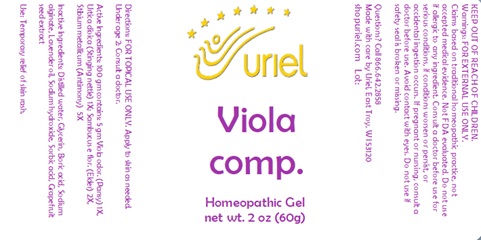 DRUG LABEL: Viola comp.
NDC: 48951-9359 | Form: GEL
Manufacturer: Uriel Pharmacy Inc.
Category: homeopathic | Type: HUMAN OTC DRUG LABEL
Date: 20231107

ACTIVE INGREDIENTS: SAMBUCUS NIGRA FLOWERING TOP 2 [hp_X]/1 g; ANTIMONY 5 [hp_X]/1 g; URTICA DIOICA 1 [hp_X]/1 g; VIOLA ODORATA FLOWERING TOP 1 [hp_X]/1 g
INACTIVE INGREDIENTS: BORIC ACID; SODIUM HYDROXIDE; WATER; SODIUM ALGINATE; SORBIC ACID; GLYCERIN; CITRUS PARADISI SEED; LAVENDER OIL

Viola comp.

INDICATIONS AND USAGE

Directions: FOR TOPICAL USE ONLY.

DOSAGE AND ADMINISTRATION

Apply to skin as needed. Under age 2: Consult a doctor.

ACTIVE INGREDIENT

Active Ingredients: 100 gm contains: 5 gm Viola odor. (Pansy) 1X, Urtica dioica (Stinging nettle) 1X; Sambucus e flor. (Elder) 2X,
Stibium metallicum (Antimony) 5X

INACTIVE INGREDIENT

Inactive Ingredients: Distilled water, Glycerin, Boric Acid, Sodium alginate, Lavender oil, Sodium hydroxide, Sorbic acid, Grapefruit seed extract

PURPOSE

Use: Temporary relief of skin rash.

KEEP OUT OF REACH OF CHILDREN.

Warnings: FOR EXTERNAL USE ONLY.
Claims based on traditional homeopathic practice, not accepted medical evidence. Not FDA evaluated.
Do not use if allergic to any ingredient. Consult a doctor before use for serious conditions, if conditions worsen or persist,
or accidental ingestion occurs. If pregnant or nursing, consult a doctor before use. Avoid contact with eyes. Do not use if safety
Seal is broken or missing.

Questions? Call 866.642.2858
Made with care by Uriel, East Troy, WI 53120
shopuriel.com Lot: